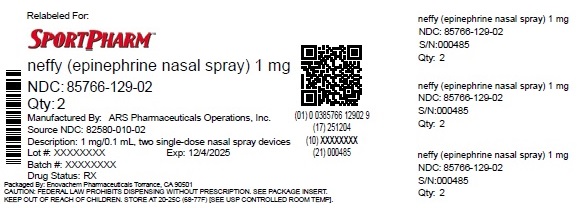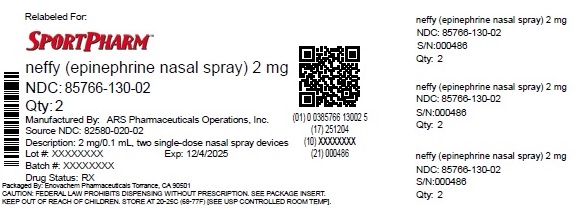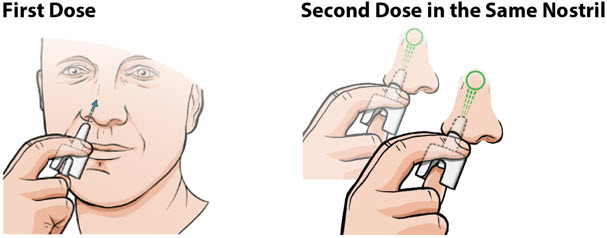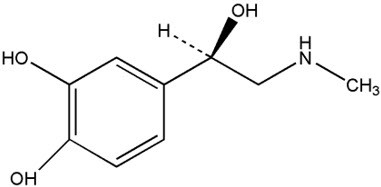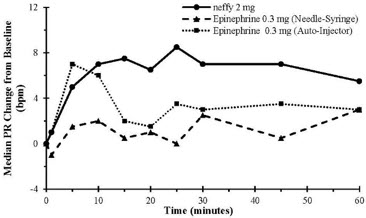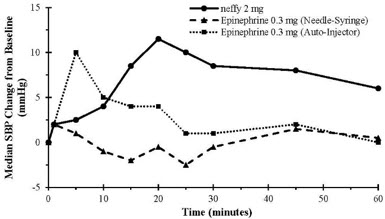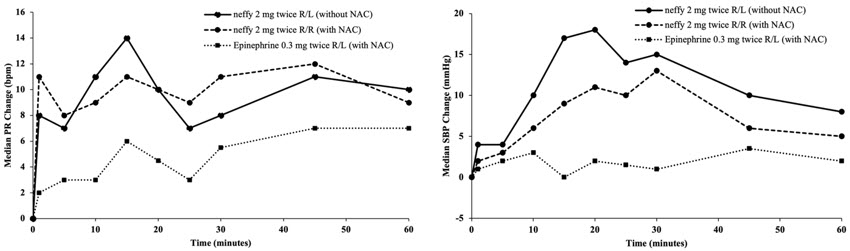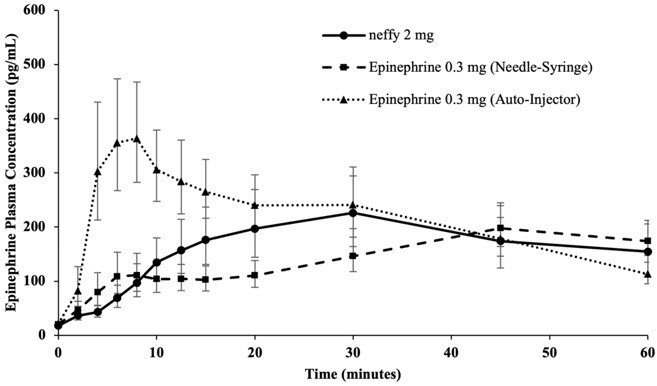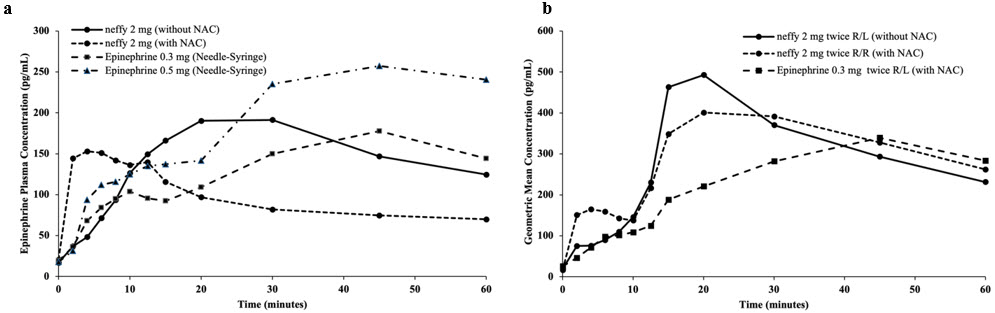 DRUG LABEL: neffy
NDC: 85766-130 | Form: SPRAY
Manufacturer: Sportpharm, Inc. dba Sportpharm
Category: prescription | Type: HUMAN PRESCRIPTION DRUG LABEL
Date: 20251206

ACTIVE INGREDIENTS: EPINEPHRINE 2 mg/100 uL
INACTIVE INGREDIENTS: N-DODECYL .BETA.-D-MALTOSIDE 0.275 mg/100 uL; SODIUM CHLORIDE; EDETATE SODIUM; BENZALKONIUM CHLORIDE; SODIUM METABISULFITE; HYDROCHLORIC ACID; SODIUM HYDROXIDE; WATER

HIGHLIGHTS OF PRESCRIBING INFORMATION

These highlights do not include all the information needed to use NEFFY®safely and effectively. See full prescribing information for NEFFY®.
NEFFY®(epinephrine nasal spray)
Initial U.S. Approval: 1939

RECENT MAJOR CHANGES

Indications (1) | 3/2025
Dosage and Administration (2.1) | 3/2025

1 INDICATIONS AND USAGE

Neffy is an alpha and beta-adrenergic receptor agonist indicated for emergency treatment of type I allergic reactions, including anaphylaxis, in adult and pediatric patients 4 years of age and older who weigh 15 kg or greater. (1)

2 DOSAGE AND ADMINISTRATION

The recommended dosage for patients 4 years of age and older who weigh 15 kg or greater is based on weight. Neffy is for nasal administration. (2.1)

Recommended Dosage
Patient's Weight | Dosage
30 kg or Greater | One spray of neffy 2 mg
15 kg to less than 30 kg | One spray of neffy 1 mg

In absence of clinical improvement or if symptoms worsen after initial treatment, administer a second dose of neffy in the same nostril with a new nasal spray starting 5 minutes after the first dose. (2.1)

- Advise patients when to seek emergency medical assistance for close monitoring of the anaphylactic episode and in the event further treatment is required. (2.1)
- It is recommended that patients are prescribed and have immediate access to two neffy nasal sprays at all times.
- See full prescribing information for administration instructions. (2.2)

3 DOSAGE FORMS AND STRENGTHS

Nasal spray:

- 1 mg/0.1 mL of epinephrine per spray (3)
- 2 mg/0.1 mL of epinephrine per spray (3)

4 CONTRAINDICATIONS

None (4)

5 WARNINGS AND PRECAUTIONS

- Absorption of neffy may be affected by underlying structural and anatomical nasal conditions. (5.1)
- Administer with caution in patients with heart disease; may aggravate angina pectoris or produce ventricular arrhythmias. (5.2)
- May aggravate certain coexisting conditions. (5.2)
- The presence of a sulfite in this product should not deter use. (5.3)

6 ADVERSE REACTIONS

Most common adverse reactions are:

- Adults (incidence ≥ 2%): nasal discomfort, headache, rhinorrhea, dizziness, nausea, vomiting, and throat irritation. (6)
- Pediatric patients 4 years of age and older who weigh 15 kg or greater (incidence ≥10%): nasal discomfort, nasal congestion, paresthesia, rhinorrhea, sneezing, upper respiratory tract congestion, epistaxis, rhinalgia, nasal dryness, dry throat, fatigue, and feeling jittery. (6)

To report SUSPECTED ADVERSE REACTIONS, contact ARS Pharmaceuticals Operations, Inc. at 1-877-MY-NEFFY (877-696-3339) or FDA at 1-800-FDA-1088 or www.fda.gov/medwatch.

7 DRUG INTERACTIONS

- Neffy may alter nasal mucosa for up to 2 weeks after administration and increase systemic absorption of nasal products, including neffy. (7.1)
- Cardiac glycosides, diuretics or anti-arrhythmics: observe for development of cardiac arrhythmias. (7.2)
- Tricyclic antidepressants, monoamine oxidase inhibitors, levothyroxine sodium, certain antihistamines, and catechol-O-methyl transferase inhibitors may potentiate effects of epinephrine. (7.3)
- Beta-adrenergic blocking drugs antagonize cardiostimulating and bronchodilating effects of epinephrine. (7.4)
- Alpha-adrenergic blocking drugs antagonize vasoconstricting and hypertensive effects of epinephrine. (7.4)
- Ergot alkaloids may reverse the pressor effects of epinephrine. (7.4)

8 USE IN SPECIFIC POPULATIONS

Elderly patients may be at greater risk of developing adverse reactions. (8.5)

FULL PRESCRIBING INFORMATION

1 INDICATIONS AND USAGE

Neffy is indicated for emergency treatment of type I allergic reactions, including anaphylaxis, in adult and pediatric patients aged 4 years and older who weigh 15 kg or greater.

2 DOSAGE AND ADMINISTRATION

2.1 Recommended Dosage

The recommended dosage for patients aged 4 years and older who weigh 15 kg or greater is based on weight and the dosage is provided in Table 1. For nasal administration [see Dosage and Administration (2.2)] .

Table 1: Recommended Dosage of Neffy Based on Patient's Weight
Patients Weight | Dosage
30 kg or Greater | One spray of neffy 2 mg
15 kg to less than 30 kg | One spray of neffy 1 mg

In the absence of clinical improvement or if symptoms worsen after the initial treatment, a second dose of neffy may be administered in the same nostril with a second nasal spray starting 5 minutes after the first dose.

- Advise patients when to seek emergency medical assistance for close monitoring of the anaphylactic episode and in the event further treatment is required.
- It is recommended that patients are prescribed and have immediate access to two neffy nasal sprays at all times.

2.2 Administration Instructions

- Neffy is for nasal use only.
- Each neffy nasal spray is for single use and delivers the entire dose upon activation.
- Do not prime or attempt to reuse neffy for more than one administration.
- Administer neffy by inserting the nozzle of the nasal spray fully into one nostril until fingers touch the nose (see Figure 1).
- Hold the nasal spray straight into the nose - do not angle the nasal spray to the inside septum or outer wall of the nose as some medication may be lost.
- Press the plunger firmly to activate.
- Avoid sniffing during and after administration.
- If a second dose of neffy is needed, administer a new nasal spray into the same nostril starting 5 minutes after the first dose (see Figure 1).
- More than two sequential doses of epinephrine should be administered under direct medical supervision.
- Refer patients and caregivers to the Instructions for Usefor detailed administration instructions.

Figure 1: Administration of Neffy

If neffy is frozen and is needed in an emergency, do not wait to thaw, seek emergency medical care immediately [see How Supplied/Storage and Handling (16)].

3 DOSAGE FORMS AND STRENGTHS

Nasal spray:

- 1 mg/0.1 mL of epinephrine per spray in a single-dose nasal spray
- 2 mg/0.1 mL of epinephrine per spray in a single-dose nasal spray

4 CONTRAINDICATIONS

None.

5 WARNINGS AND PRECAUTIONS

5.1 Potential Altered Absorption of Neffy in Patients with Underlying Structural or Anatomical Nasal Conditions

Clinical pharmacology studies with neffy included subjects with history of allergic rhinitis, but did not include subjects with underlying structural and anatomical nasal conditions (e.g., polyps, history of nasal fractures or injuries, or history of nasal surgery). Absorption of neffy may be affected by underlying structural and anatomical nasal conditions. Consider use of other epinephrine products given by other routes of administration for patients with underlying structural or anatomical nasal conditions.

5.2 Risks Associated with Use of Epinephrine in Certain Coexisting Conditions

Some patients may be at greater risk for developing adverse reactions after epinephrine administration. Despite these concerns, it should be recognized that the presence of these conditions is not a contraindication to epinephrine administration in an acute, life-threatening situation. Therefore, patients with these conditions, and/or any other person who might be in a position to administer neffy to a patient experiencing anaphylaxis should be carefully instructed in regard to the circumstances under which epinephrine should be used.

Epinephrine should be administered with caution to patients who have heart disease, including patients with cardiac arrhythmias, coronary artery disease, or hypertension. In such patients, or in patients who are on drugs that may sensitize the heart to arrhythmias, epinephrine may precipitate or aggravate angina pectoris, as well as produce ventricular arrhythmias [see Drug Interactions (7)and Adverse Reactions (6)] .

Epinephrine can temporarily exacerbate the underlying condition or increase symptoms in patients with the following: hyperthyroidism, Parkinson's disease, diabetes, renal impairment. Epinephrine should be administered with caution in patients with these conditions, including elderly patients and pregnant women.

5.3 Allergic Reactions Associated with Sulfite

Epinephrine is the preferred treatment for serious allergic or other emergency situations even though neffy contains sodium metabisulfite, a sulfite that may in other products cause allergic-type reactions including anaphylactic symptoms or life-threatening or less severe asthmatic episodes in certain susceptible persons. The alternatives to using epinephrine in a life-threatening situation may not be satisfactory. The presence of a sulfite(s) in neffy should not deter administration of the drug for treatment of serious allergic or other emergency situations.

6 ADVERSE REACTIONS

The following clinically significant adverse reactions are described elsewhere in the labeling:

- Risks Associated with Use of Epinephrine in Certain Coexisting Conditions [see Warnings and Precautions (5.2)]
- Allergic Reactions Associated with Sulfite [see Warnings and Precautions (5.3)]

Because clinical trials are conducted under widely varying conditions, adverse reaction rates observed in the clinical trials of a drug cannot be directly compared to rates in the clinical trials of another drug and may not reflect the rates observed in practice.

Adverse Reactions with Neffy in Adult Subjects

The safety of neffy 2 mg is based on four clinical pharmacology studies in 175 healthy adults and adults with type I allergy without anaphylaxis, who did not have structural or anatomical nasal conditions [see Clinical Pharmacology (12.2, 12.3)] . The four clinical pharmacology studies were designed to compare the pharmacokinetic (PK) and pharmacodynamic (PD) profiles of one dose of neffy 2 mg sprayed into one nostril or two doses of neffy 2 mg sprayed into either the same or opposite nostril, administered 10 minutes apart, with PK and PD profiles of one or two dose(s) of epinephrine injection administered intramuscularly. The common adverse reactions that occurred with neffy 2 mg after one and two dose(s) are listed in Table 2.

Table 2: Adverse Reactions with One or Two Dose(s) of Neffy with Incidence Greater than or Equal to 2% in Adults [Studies 1, 2, 3, and 4]
Adverse Reaction [Data include subjects with nasal allergen challenge induced rhinitis] | Neffy 2 mg One Dose |  | Neffy 2 mg Two Doses [Two nasal doses of neffy 2 mg were administered 10 minutes apart]
Adverse Reaction [Data include subjects with nasal allergen challenge induced rhinitis] | N = 134 [The trials used a crossover design and therefore the total number of subjects do not match the number of unique subjects (n = 175)] |  | N = 85
Adverse Reaction [Data include subjects with nasal allergen challenge induced rhinitis]
Nasal discomfort | 13 | (10%) | 11 | (13%)
Headache | 8 | (6%) | 15 | (18%)
Rhinorrhea | 4 | (3%) | 6 | (7%)
Dizziness | 4 | (3%) | 2 | (2%)
Nausea | 4 | (3%) | 2 | (2%)
Vomiting | 3 | (2%) | 2 | (2%)
Throat irritation | 2 | (2%) | 16 | (19%)
Feeling jittery | 1 | (1%) | 9 | (11%)
Abdominal pain | 1 | (1%) | 3 | (4%)
Tremor | 0 | (0%) | 7 | (8%)
Nasal pruritus | 0 | (0%) | 3 | (4%)
Sneezing | 0 | (0%) | 3 | (4%)
Gingival pain | 0 | (0%) | 3 | (4%)
Hypoesthesia oral | 0 | (0%) | 3 | (4%)
Nasal Congestion | 0 | (0%) | 2 | (2%)

Adverse Reactions with Neffy in Pediatric Subjects 4 Years of Age and Older Weighing 15 kg or Greater

A single-arm clinical pharmacology study (Study 5) in pediatric subjects 4 to 17 years of age who weigh 15 kg or greater with type I allergy without anaphylaxis was conducted to assess the pharmacokinetic/pharmacodynamic (PK/PD) of neffy 1 mg and 2 mg [see Clinical Pharmacology (12.2, 12.3)] . Pediatric subjects (n=21) who weigh 30 kg or greater received one nasal dose of neffy 2 mg and common adverse reactions reported in these subjects include nasal discomfort (19%), intranasal paresthesia (19%), rhinorrhea (19%), sneezing (14%), epistaxis (10%), rhinalgia (10%), paresthesia (10%), fatigue (10%), and feeling jittery (10%). Pediatric subjects (n=21) who weigh 15 to less than 30 kg received one nasal dose of neffy 1 mg and common adverse reactions reported in these subjects include nasal congestion (19%), upper respiratory tract congestion (14%), dry throat (10%), nasal dryness (10%), and paresthesia (10%).

Adverse Reactions from Postapproval Use of Epinephrine Products

The following adverse reactions have been identified during postapproval use of epinephrine. Because these reactions are reported voluntarily from a population of uncertain size, it is not always possible to reliably estimate their frequency or establish a causal relationship to drug exposure.

Cardiovascular: angina, arrhythmias (including fatal ventricular fibrillation), cerebral hemorrhage, hypertension, pallor, palpitations, tachyarrhythmia, tachycardia, vasoconstriction, ventricular ectopy, and stress cardiomyopathy

Metabolism and Nutrition Disorders: transient hyperglycemia, sweating

Neurological: disorientation, impaired memory, panic, psychomotor agitation, sleepiness, tingling, weakness

Psychiatric: anxiety, apprehensiveness, restlessness

Respiratory: respiratory difficulties

7 DRUG INTERACTIONS

7.1 Potential Increased Exposure of Nasal Spray Drugs

Neffy may alter nasal mucosa for up to 2 weeks after administration, and thus may increase systemic absorption of nasal products, including neffy, potentially increasing the risk of adverse reactions associated with these products.

7.2 Drugs Increasing Risk of Cardiac Arrhythmias

Patients who receive epinephrine while concomitantly taking cardiac glycosides, diuretics, or anti-arrhythmics should be observed carefully for the development of cardiac arrhythmias [see Warnings and Precautions (5.2)and Adverse Reactions (6)] .

7.3 Drugs Potentiating Effects of Epinephrine

The effects of epinephrine may be potentiated by tricyclic antidepressants, monoamine oxidase inhibitors, levothyroxine sodium, certain antihistamines, notably chlorpheniramine, tripelennamine, and diphenhydramine, and catechol-O-methyl transferase (COMT) inhibitors such as entacapone.

7.4 Drugs Antagonizing Effects of Epinephrine

The cardiostimulating and bronchodilating effects of epinephrine are antagonized by beta- adrenergic blocking drugs, such as propranolol.

The vasoconstricting and hypertensive effects of epinephrine are antagonized by alpha- adrenergic blocking drugs, such as phentolamine.

Ergot alkaloids may also reverse the pressor effects of epinephrine.

8 USE IN SPECIFIC POPULATIONS

8.1 Pregnancy

Risk Summary

Prolonged experience with epinephrine use in pregnant women over several decades, based on published literature, have not identified a drug associated risk of major birth defects, miscarriage or adverse maternal or fetal outcomes. There are risks to the mother and fetus associated with anaphylaxis, and treatment with epinephrine should not be delayed (see Clinical Considerations). In animal reproduction studies, epinephrine administered by the subcutaneous route to pregnant rabbits, mice, and hamsters, during the period of organogenesis, resulted in adverse developmental effects (including gastroschisis, and embryonic lethality, and delayed skeletal ossification) at doses approximately 2 times the maximum recommended daily intramuscular, subcutaneous, or intravenous dose (see Data).

The background risk of major birth defects and miscarriage for the indicated population is unknown. All pregnancies have a background risk of birth defect, loss, or other adverse outcomes. In the United States general population, the estimated background risk of major birth defects and miscarriage in clinically recognized pregnancies is 2% to 4% and 15% to 20%, respectively.

Clinical Considerations

Disease-Associated Maternal and Embryo/Fetal Risk

During pregnancy, anaphylaxis can be catastrophic and can lead to hypoxic-ischemic encephalopathy and permanent central nervous system damage or death in the mother and, more commonly, in the fetus or neonate. Treatment of anaphylaxis during pregnancy should not be delayed.

Data

Animal Data

In an embryofetal development study with pregnant rabbits dosed during the period of organogenesis (on days 3 to 5, 6 to 7 or 7 to 9 of gestation), epinephrine caused teratogenic effects (including gastroschisis) at doses approximately 15 times the maximum recommended intramuscular, subcutaneous, or intravenous dose (on a mg/m^2basis at a maternal subcutaneous dose of 1.2 mg/kg/day for two to three days). Animals treated on days 6 to 7 had decreased number of implantations.

In an embryofetal development study, pregnant mice were administered epinephrine (0.1 to 10 mg/kg/day) on Gestation Days 6 to 15. Teratogenic effects, embryonic lethality, and delays in skeletal ossification were observed at approximately 3 times the maximum recommended intramuscular, subcutaneous, or intravenous dose (on a mg/m^2basis at maternal subcutaneous dose of 1 mg/kg/day for 10 days). These effects were not seen in mice at approximately 2 times the maximum recommended daily intramuscular or subcutaneous dose (on a mg/m^2basis at a subcutaneous maternal dose of 0.5 mg/kg/day for 10 days).

In an embryofetal development study with pregnant hamsters dosed during the period of organogenesis from gestation days 7 to 10, epinephrine produced reductions in litter size and delayed skeletal ossification at doses approximately 2 times the maximum recommended intramuscular, subcutaneous, or intravenous dose (on a mg/m^2basis at a maternal subcutaneous dose of 0.5 mg/kg/day).

8.2 Lactation

Risk Summary

There are no data on the presence of epinephrine or its metabolite in human milk, the effects on the breastfed infant, or the effects on human milk production. However, due to its poor oral bioavailability and short half-life, transfer of epinephrine into breastmilk is expected to be low. Treatment for anaphylaxis in breastfeeding patients should not be delayed.

8.4 Pediatric Use

The safety and effectiveness of neffy for emergency treatment of type I allergic reactions, including anaphylaxis, have been established in pediatric patients aged 4 years and older who weigh 15 kg or greater. Use of neffy for this indication is supported by extrapolation from the clinical pharmacology studies in adults that compared the PK/PD profile of neffy to epinephrine injection products with established safety and effectiveness for this indication and clinical pharmacology data (Study 5) in pediatric patients aged 4 years and older who weigh 15 kg or greater [see Adverse Reactions (6)and Clinical Pharmacology (12.2, 12.3)].

The safety and effectiveness of neffy have not been established in pediatric patients less than 4 years of age and who weigh less than 15 kg.

8.5 Geriatric Use

Clinical pharmacology studies of neffy for the emergency treatment of type I allergic reactions, including anaphylaxis, did not include a sufficient number of subjects aged 65 and over to determine whether they respond differently from younger adult subjects. However, other reported clinical experience with use of epinephrine for the treatment of anaphylaxis has identified that geriatric patients may be particularly sensitive to the effects of epinephrine. Neffy should be administered with caution in elderly patients who are at greater risk for developing adverse reactions after epinephrine administration.

10 OVERDOSAGE

Overdosage of epinephrine has been reported to produce extremely elevated arterial pressure, which may result in cerebrovascular hemorrhage, particularly in elderly patients. Overdosage may also result in pulmonary edema because of peripheral vascular constriction together with cardiac stimulation. Epinephrine overdosage can also cause transient bradycardia followed by tachycardia which may be accompanied by fatal cardiac arrhythmias; premature ventricular contractions followed by multifocal ventricular tachycardia; atrial tachycardia and occasionally by atrioventricular block; extreme pallor and coldness of the skin; metabolic acidosis; kidney failure.

Epinephrine is rapidly inactivated in the body and treatment following overdosage with epinephrine is primarily supportive. Treatment of epinephrine associated pulmonary edema consists of a rapidly acting alpha-adrenergic blocking drug (such as phentolamine mesylate) and respiratory support. Treatment of epinephrine associated arrhythmias consists of administration of a beta-adrenergic blocking drug (such as propranolol). If necessary, pressor effects may be counteracted by rapidly acting vasodilators or α-adrenergic blocking drugs. If prolonged hypotension follows such measures, it may be necessary to administer another pressor drug.

Consider contacting the Poison Help line (1-800-222-1222) or a medical toxicologist for additional overdosage management recommendations.

11 DESCRIPTION

Neffy contains epinephrine, a sympathomimetic catecholamine. Chemically, epinephrine is (-)-3,4-dihydroxy-α-[(methylamino)methyl] benzyl alcohol with molecular weight of 183.21 g/mol and the following structure:

Neffy (epinephrine nasal spray) is supplied as single-dose nasal sprays containing 1 mg or 2 mg of epinephrine in 0.1 mL solution for nasal administration.

Inactive ingredients include benzalkonium chloride, disodium edetate, n-dodecyl beta-D-maltoside, sodium chloride, sodium metabisulfite, and hydrochloric acid or sodium hydroxide to adjust pH, in water for injection. The pH range is approximately 3 to 5.5.

12 CLINICAL PHARMACOLOGY

12.1 Mechanism of Action

Epinephrine acts on both alpha and beta-adrenergic receptors.

Through its action on alpha-adrenergic receptors, epinephrine lessens the vasodilation and increased vascular permeability that occurs during anaphylaxis, which can lead to loss of intravascular fluid volume and hypotension.

Through its action on beta-adrenergic receptors, epinephrine causes bronchial smooth muscle relaxation and helps alleviate bronchospasm, wheezing and dyspnea that may occur during anaphylaxis.

Epinephrine alleviates pruritus, urticaria, and angioedema. It may also relieve gastrointestinal and genitourinary symptoms associated with anaphylaxis because of its relaxer effects on the smooth muscle of the stomach, intestine, uterus, and urinary bladder.

12.2 Pharmacodynamics

Four clinical pharmacology studies of neffy in adults and one clinical pharmacology study in pediatric subjects who weigh 30 kg or greater are described below. All doses were administered by study staff unless otherwise stated.

Systolic Blood Pressure and Pulse Rate in Healthy Adult Subjects (Study 1)

Study 1 was conducted in healthy adult subjects (N=42) that compared the pharmacokinetics (PK) [see Clinical Pharmacology (12.3)] and pharmacodynamics (PD) (i.e., pulse rate (PR) and systolic blood pressure (SBP)) of epinephrine following:

- One nasal dose of neffy 2 mg to one intramuscular dose of epinephrine injection 0.3 mg (using a needle-syringe product and an auto-injector product).
- Two nasal doses of neffy 2 mg, administered 10 minutes apart, into either same naris or opposite nares to two intramuscular doses of epinephrine injection 0.3 mg (using an auto-injector) administered 10 minutes apart.

In Study 1, SBP and PR responses were assessed as change from baseline over 60 minutes.

Results following one dose of all epinephrine products demonstrated an increase from baseline SBP and PR as shown in Figure 2. The median/mean increase in SBP and PR for neffy were within the range of both epinephrine injection treatments during the first 10 minutes post-dose. Thereafter, the median/mean SBP and PR responses for neffy were higher than both epinephrine injection treatments through 60 minutes post-dose.

Figure 2: Median Pulse Rate (PR) and Systolic Blood Pressure (SBP) Change from Baseline Following One Dose of Epinephrine in Healthy Subjects [Study 1]

Results following two nasal doses of neffy (in the same naris or opposite nares) in comparison to two intramuscular doses of epinephrine injection (using an auto-injector) showed a similar trend in median/mean SBP and PR responses.

The clinical meaning of SBP and PR responses observed in healthy subjects is unclear in the context of treating anaphylaxis.

Systolic Blood Pressure and Pulse Rate in Adult Patients with Type I Allergy without Anaphylaxis (Study 2)

Study 2 was conducted in adult patients with type I allergy without anaphylaxis (N=42) that compared the PK and PD of epinephrine following self-administered one nasal dose of neffy 2 mg to staff-administered one intramuscular dose of epinephrine injection 0.3 mg (using a needle-syringe product).

In Study 2, SBP and PR responses were assessed as a change from baseline over 60 minutes. The SBP and PR responses results in Study 2 were similar to Study 1.

Systolic Blood Pressure and Pulse Rate in Adult Patients with Nasal Allergen Challenge Induced Rhinitis (Study 3 and 4)

Study 3 and Study 4 were conducted in adult subjects with seasonal allergic rhinitis outside of allergy season (neffy is not approved for the treatment of allergic rhinitis). Subjects were required to have seasonal allergic rhinitis which was confirmed with a nasal allergen challenge (NAC) during screening and did not have any allergy symptoms prior to treatment. Allergic rhinitis symptoms were induced by spraying the known allergen into the subject's nostrils in which a minimum Total Nasal Symptom Score (TNSS) of ≥ 5 out of 12, with a congestion component of ≥ 2 out of 3 had to be reached.

Study 3 enrolled 36 subjects. In this cross-over study, subjects received epinephrine as each of the following:

- One nasal dose of neffy 2 mg without nasal allergen challenge (NAC).
- One nasal dose of neffy 2 mg after undergoing NAC to induce rhinitis/nasal congestion.
- One intramuscular dose of epinephrine injection 0.3 mg (using a needle syringe) without NAC.
- One intramuscular dose of epinephrine injection 0.5 mg (using a needle syringe) without NAC.

In Study 3, SBP and PR responses were assessed as a change from baseline over 60 minutes. Results showed the following:

- Median SBP and PR for neffy with NAC initially increased from baseline, but the median responses were lower than the use of neffy without NAC after 5 to 15 minutes post-dose.
- Median SBP response for neffy with NAC was initially higher than the median SBP response for the intramuscular epinephrine injection without NAC through 20 minutes, after which the median SBP response for neffy with NAC became comparable to the epinephrine injection without NAC through 60 minutes post-dose.
- Median PR response for neffy with NAC was initially higher than epinephrine injection without NAC during the first 5 minutes post-dose, but then was numerically lower than the median PR response for epinephrine injection without NAC through 60 minutes post-dose.

Study 4 enrolled 43 subjects. In this cross-over study, subjects received the following:

- Two nasal doses of neffy 2 mg (in the opposite nares) without NAC administered 10 minutes apart.
- Two intramuscular doses of epinephrine injections 0.3 mg (using a needle-syringe) without NAC administered 10 minutes apart.
- Two nasal doses of neffy 2 mg (either in the same naris or opposite nares) after NAC to induce allergic rhinitis/nasal congestion administered 10 minutes apart.
- Two intramuscular doses of epinephrine injections 0.3 mg (using a needle-syringe) after NAC to induce allergic rhinitis/nasal congestion administered 10 minutes apart.

In Study 4, SBP and PR responses were assessed as a change from baseline over 60 minutes. Results showed the following:

- Median SBP and PR responses for two nasal doses of neffy (in the same naris) after NAC increased from baseline and remained higher than median SBP and PR response for two intramuscular doses of epinephrine injections after NAC through 60 minutes post-first dose (Figure 3).
- Median SBP response for two nasal doses of neffy (in the opposite nares) after NAC was higher than for two intramuscular doses of epinephrine injections after NAC within 30 minutes post-first dose, but then decreased and became numerically lower afterwards. Median PR response for two nasal doses of neffy (in the opposite nares) after NAC was also initially higher than two intramuscular doses of epinephrine injection after NAC and became lower after 40 minutes post-first dose.

Figure 3: Median Change from Baseline for Pulse Rate (PR) and Systolic Blood Pressure (SBP) Following Two Doses of Epinephrine Administered 10 Minutes Apart in Subjects with and without Nasal Allergen Challenge (NAC) Induced Rhinitis [Study 4]

R/L: First dose administered in right naris followed by second dose administered in left naris 10 minutes apart.
R/R: First dose administered in right naris followed by second dose administered in right naris 10 minutes apart.
Epinephrine 0.3 mg was administered using needle-syringe product

Systolic Blood Pressure and Pulse Rate in Pediatric Patients Aged 4 Years and Older Weighing 15 kg or Greater with Type I Allergy without Anaphylaxis (Study 5)

Study 5 was a single-arm study conducted in pediatric patients who weighed 15 kg or greater (age range: 4 to 17 years) with type I allergy without anaphylaxis (N=42) that assessed the PK and PD of epinephrine following one nasal dose of neffy 1 mg (for subjects who weigh 15 kg to < 30 kg) and 2 mg (for subjects who weigh 30 kg or greater). The median change in SBP from baseline over the 60 minutes post-dose were numerically lower than in adults who received neffy 2 mg in Study 1 and 2, while the median change in PR from baseline over 60 minutes post-dose was within the range of adults who received neffy 2 mg in Study 1 and 2.

12.3 Pharmacokinetics

Pharmacokinetics assessments were performed in the clinical pharmacology studies described in the Pharmacodynamicssubsection [see Clinical Pharmacology (12.2)] .

Pharmacokinetics in Healthy Adult Subjects (Study 1)

See Pharmacodynamics (12.2)for a description for Study 1.

Following one nasal dose of neffy 2 mg in Study 1, the geometric mean plasma epinephrine concentration-time profile was overall within the range of that following one intramuscular dose of epinephrine injection 0.3 mg (using a needle-syringe product and an auto-injector product) 60 minutes post-dose. The epinephrine plasma concentration versus time profiles are shown in Figure 4. The pharmacokinetic parameters of epinephrine are summarized in Table 3.

Figure 4: Epinephrine Geometric Mean (90% Confidence Interval) Plasma Concentration-Time Profiles Following One Dose of Epinephrine in Healthy Subjects [Study 1]

Table 3: Geometric Mean (CV%) Plasma PK Parameters Following One Dose of Epinephrine in Healthy Subjects [Study 1]
Product | Pharmacokinetic Parameters [%CV]
Product | GeoMean Cmax (pg/mL) | Median Tmax (min) | GeoMean AUC0-10min(min*pg/mL) [Note: Based on within-study comparison results from Studies 1, 2, and 3, the epinephrine exposures in the first 10 minutes following neffy administration were generally within the range observed following epinephrine injection 0.3 mg (needle-syringe)] | GeoMean AUC0-20min(min*pg/mL) | GeoMean AUC0-45min(min*pg/mL) | GeoMean AUC0-60min (min*pg/mL)
Epinephrine 0.3 mg (Needle-Syringe) (N=42) | 283 [62] | 45 | 879 [120] | 2032 [89] | 6172 [67] | 9217 [59]
Neffy 2 mg (N=42) | 341 [114] | 30 | 704 [92] | 2548 [102] | 8156 [115] | 10916 [116]
Epinephrine 0.3 mg (Auto-Injector) (N=42) | 604 [79] | 8 | 2771 [115] | 5818 [83] | 12227 [60] | 14762 [57]

Following two nasal doses of neffy 2 mg, administered 10 minutes apart, either into the same naris or opposite nares under normal nasal conditions, the Cmaxand AUC0-60 minincreased approximately dose proportionally compared to one nasal dose of neffy 2 mg in healthy adults. The systemic exposures of two doses of neffy 2 mg administered into the same naris or the opposite nares under normal nasal conditions were generally similar and comparable to that of two intramuscular injections of epinephrine 0.3 mg (using an auto-injector product), administered 10 minutes apart, after 20 to 30 minutes post-dose.

Pharmacokinetics in Adult Patients with Type I Allergy without Anaphylaxis (Study 2)

See the Pharmacodynamics (12.2)for a description for Study 2.

The geometric mean plasma epinephrine concentration time profile following one self-administered nasal dose of neffy 2 mg was numerically higher than that of one staff-administered intramuscular dose of epinephrine injection 0.3 mg (using a needle-syringe product) during the first 60 minutes post-dose (Study 2). The systemic exposure of epinephrine following one self-administered dose of neffy 2 mg in adult patients with type I allergy without anaphylaxis was similar to that following one staff-administered dose of neffy 2 mg in healthy adult subjects from Study 1.

Pharmacokinetics in Adult Patients with Nasal Allergen Challenge Induced Rhinitis (Studies 3 and 4)

See the Pharmacodynamics (12.2)for a description of Studies 3 and 4.

- In Study 3, the geometric mean plasma epinephrine concentrations in patients who received one nasal dose of neffy 2 mg after NAC initially increased more rapidly during the first 5 minutes compared to those that received one nasal dose of neffy 2 mg without NAC and one intramuscular dose of epinephrine injection (0.3 mg or 0.5 mg) without NAC. The geometric mean plasma epinephrine concentrations of patients who received neffy 2 mg with NAC declined after approximately 10 minutes post-dose and became numerically lower than both the neffy 2 mg without NAC and epinephrine injection (0.3 mg or 0.5 mg) after 20 minutes post-dose (Figure 5a).
- In Study 4, the geometric mean of plasma epinephrine concentrations in patients who received two nasal doses of neffy 2 mg, administered 10 minutes apart, (in the same naris) after NAC were higher than those who received two intramuscular doses of epinephrine injection 0.3 mg, administered 10 minutes apart, with or without NAC up to 40 minutes post-first dose and then became similar afterwards (Figure 5b). The geometric mean plasma epinephrine concentrations of patients who received two doses of neffy 2 mg, administered 10 minutes apart, (in the opposite nares) after NAC, were initially higher than those who received two intramuscular doses of epinephrine injection 0.3 mg, administered 10 minutes apart, with or without NAC for around 25 to 30 minutes post-first dose, but became lower afterwards.

Figure 5: Epinephrine Geometric Mean Plasma Concentration-Time Profiles Following One or Two Dose(s) of Epinephrine in Adult Subjects with and without Nasal Allergen Challenge Induced Rhinitis [Study 3 and Study 4]

a: Epinephrine geometric mean plasma concentration-time profiles following one dose of epinephrine in Study 3
b: Epinephrine geometric mean plasma concentration-time profiles following two doses of epinephrine in Study 4
R/L: First dose administered in right naris followed by second dose administered in left naris 10 minutes apart.
R/R: First dose administered in right naris followed by second dose administered in right naris 10 minutes apart.
Epinephrine 0.3 mg was administered using needle-syringe product

Pharmacokinetics in Pediatric Patients Aged 4 Years and Older Weighing 15 kg or Greater with Type I Allergy without Anaphylaxis (Study 5)

See the Pharmacodynamics (12.2)for a description for Study 5.

In pediatric patients with type I allergy without anaphylaxis who weigh 15 kg or greater (age range: 4 to 17 years), following one nasal dose of neffy 1 mg (for subjects who weigh 15 kg to < 30 kg) or 2 mg (for subjects who weigh 30 kg or greater) (Study 5), the geometric mean plasma epinephrine concentration time profiles for both weight groups were numerically higher than that of adults who received neffy 2 mg (Study 1 and 2).

Elimination:

Metabolism:Epinephrine is extensively metabolized with only a small amount excreted unchanged.

Epinephrine is rapidly degraded to vanillylmandelic acid, an inactive metabolite, by monoamine oxidase and catechol-O-methyltransferase that are abundantly expressed in the liver, kidneys and other extraneuronal tissues. The tissues with the highest contribution to removal of circulating exogenous epinephrine are the liver (32%), kidneys (25%), skeletal muscle (20%), and mesenteric organs (12%).

Specific Populations:

Age:In a PK study of 45-minute epinephrine intravenous infusions given to healthy male subjects aged 20 to 25 years and healthy male subjects aged 60 to 65 years, the mean plasma metabolic clearance rate of epinephrine at steady state was greater among the older male subjects compared to younger male subjects (144.8 versus 78 mL/kg/minute, respectively, for a 0.0143 mcg/kg/minute infusion).

Body Weight:Body weight has been found to influence epinephrine PK. Higher body weight was associated with a higher plasma epinephrine clearance and a lower concentration plateau.

13 NONCLINICAL TOXICOLOGY

13.1 Carcinogenesis, Mutagenesis, Impairment of Fertility

Long-term studies to evaluate the carcinogenic potential of epinephrine have not been conducted. Epinephrine and other catecholamines have been shown to have mutagenic potential in vitro. Epinephrine was positive in the Salmonellabacterial reverse mutation assay, positive in the mouse lymphoma assay, and negative in the in vivomicronucleus assay. Epinephrine is an oxidative mutagen based on the E. coliWP2 Mutoxitest bacterial reverse mutation assay. This should not prevent the use of epinephrine where indicated [see Indications and Usage (1)] . The potential for epinephrine to impair reproductive performance has not been evaluated, but epinephrine has been shown to decrease implantation in female rabbits dosed subcutaneously with 1.2 mg/kg/day (15-fold the highest human intramuscular or subcutaneous daily dose) during gestation days 3 to 9.

13.2 Animal Toxicology and/or Pharmacology

In a single-dose nasal toxicity study, treatment of neffy in rats induced epinephrine-related histopathological changes in the nose, such as minimal ulceration of the exposed mucosa (at ≥2.3-fold the recommended clinical dose of neffy 2 mg based on local surface area), and nasal passages, such as minimal to mild necrosis in the nasal turbinate and parietal wall in the rostral-most level (at ≥1.2-fold the recommended clinical dose of neffy 2 mg based on local surface area) on day 2. These findings were often associated with minimal to mild neutrophilic inflammation and were reversible after 14 days post-dose.

16 HOW SUPPLIED/STORAGE AND HANDLING

How Supplied

Neffy (epinephrine nasal spray) is available in 1 mg and 2 mg strengths as described in Table 4.

Table 4: Neffy Strengths and Package Configurations
Strength | Package Configuration | NDC
1 mg/0.1 mL | Carton containing two (2) blister packages each with a single-dose nasal spray for 1 time use | NDC 85766-129-02 relabeled from NDC 82580-010-02
2 mg/0.1 mL | Carton containing two (2) blister packages each with a single-dose nasal spray for 1 time use | NDC 85766-130-02 relabeled from NDC 82580-020-02

Storage and Handling

Store neffy nasal spray in the blister pack until ready to use.

Store at 68°F to 77°F (20°C to 25°C). Excursions permitted up to 122°F (50°C).

Do not freeze. Neffy freezes below 5°F (-15°C). If neffy freezes, it will not deliver epinephrine.

17 PATIENT COUNSELING INFORMATION

Advise the patient to read the FDA-approved patient labeling (Patient Information and Instructions for Use).

Administration Instructions

- Advise patients and/or caregivers to store neffy nasal spray in the blister pack until ready to use.
- Neffy nasal spray is for single use and delivers the entire dose upon activation.
- Advise patients when to seek emergency medical assistance for close monitoring of the anaphylactic episode and in the event further treatment is required.
- Instruct patients and/or caregivers in the appropriate use of neffy. Administer neffy into one nostril pointing straight into the naris, press the plunger firmly to activate [see Dosage and Administration (2.2)and Instructions for Use] . If a second dose of neffy is needed, administer a new neffy nasal spray into the same nostril (ipsilateral side) starting 5 minutes after the first dose.
- Advise patients that improper dosing in the nose may result in some drug dripping out of the nose and not being available for absorption. If symptoms do not improve or worsen, patients and/or caregivers should administer a second dose of neffy in the same nostril starting 5 minutes after the first dose.

Risks Associated with Certain Coexisting Conditions

Advise patients with coexisting conditions (cardiac arrhythmia, coronary artery disease, hypertension, pulmonary edema, hyperthyroidism, renal impairment, Parkinson's disease, diabetes), for increased risks that may be associated with use of epinephrine [see Warnings and Precautions (5.2)] .

Relabeled by:

Enovachem PHARMACEUTICALS

Torrance, CA 90501

PATIENT INFORMATION
NEFFY®(ne'fee)
(epinephrine nasal spray)
For allergic emergencies (anaphylaxis)

Read this Patient Information leaflet carefully before you start using neffy and each time you get a refill. There may be new information. You, your caregiver, or others who may be in a position to administer neffy should know how to use it before you have an allergic emergency. This information does not take the place of talking with your healthcare provider about your medical condition or your treatment.

1. What is the most important information I should know about neffy?
  Neffy contains epinephrine, a medicine used to treat allergic emergencies (anaphylaxis). Anaphylaxis can be life-threatening, can happen in minutes, and can be caused by stinging and biting insects, allergy injections, foods, medicines, exercise, or other unknown causes.
  Symptoms of anaphylaxis may include:

- trouble breathing
- wheezing
- hoarseness (changes in the way your voice sounds)
- hives (raised reddened rash that may itch)
- severe itching
- swelling of your face, lips, mouth, or tongue
- skin rash, redness, or swelling
- fast heartbeat

- weak pulse
- feeling very anxious
- confusion
- stomach pain
- losing control of urine or bowel movements (incontinence)
- diarrhea or stomach cramps
- dizziness, fainting, or "passing out" (unconsciousness)

1. Always carry neffy with you because you may not know when anaphylaxis may happen. It is recommended that you carry 2 neffy devices because you may need a second dose of neffy if symptoms continue or come back. Talk to your healthcare provider if you need additional devices to keep at work, school, or other locations. Tell your family members, caregivers, and others where you keep your neffy device and how to use it before you need it. You may be unable to speak in an allergic emergency.
2. When you have an allergic emergency (anaphylaxis)
  - Use neffy right away.
  - Get emergency medical help for further treatment of the allergic emergency (anaphylaxis), if needed after using neffy. Before you receive neffy, your healthcare provider should talk to you about when to get emergency help.

What is neffy?

- Neffy is a nasal spray used to treat life-threatening, allergic emergencies including anaphylaxis in adults and children aged 4 years and older who weigh 33 pounds or more (15 kilograms or more), who are at risk for or have a history of serious allergic emergencies. Each neffy contains a single dose of epinephrine.
- Neffy is for immediate self (or caregiver) administration in an allergic emergency.
- Neffy is for people who have been prescribed this medicine by their healthcare provider.
- It is not known if neffy is safe and effective in children who weigh less than 33 pounds (15 kilograms).

Before using neffy, tell your healthcare provider about all your medical conditions, especially if you:

- have nasal problems including nasal polyps, history of injury such as a broken nose, or any past nasal surgery.
- have heart problems.
- have kidney problems.
- have low potassium levels in your blood.
- have Parkinson's disease.
- have thyroid problems.
- have high blood pressure.
- have diabetes.
- are pregnant or plan to become pregnant. It is not known if epinephrine will harm your unborn baby.
- are breastfeeding or plan to breastfeed. It is not known if epinephrine passes into your breastmilk.

Tell your healthcare provider about all the medicines you take, including prescription and over-the-counter medicines, vitamins and herbal supplements. Tell your healthcare provider of all known allergies.
Especially tell your healthcare provider if you take or use:

- other nasal sprays
- water pills (diuretics)
- medicines to treat depression such as tricyclic antidepressants or monoamine oxidase inhibitors (MAO inhibitors)
- medicines to treat abnormal heart beats (arrhythmias) such as cardiac glycosides
- medicines to treat Parkinson's disease such as catechol-O-methyl-transferase inhibitors (COMT inhibitors) and ergot alkaloids
- medicines for heart disease including alpha blockers (such as phentolamine) and beta blockers (such as propranolol)
- medicines for thyroid disease such as levothyroxine sodium
- medicines used in labor
- medicines to treat allergies such as diphenhydramine, tripelennamine or chlorpheniramine (antihistamines)

Neffy and other medicines may affect each other, causing side effects. Neffy may affect the way other medicines work, and other medicines may affect how neffy works.
Know the medicines you take. Keep a list of them to show your healthcare provider and pharmacist when you get a new medicine.
Use neffy for the treatment of anaphylaxis as prescribed by your healthcare provider, regardless of your medical conditions or medicine you take.

How should I use neffy?

- Read the Instructions for Use that come with neffy for detailed information about the right way to use the device.
- Use neffy exactly as your healthcare provider tells you to use it. Talk to your healthcare provider or pharmacist if you have questions about the use of neffy.
- Neffy is for use in the nose only. Do not spray in the eyes or mouth.
- Each neffy has 1 dose of medicine and cannot be reused. Do not test or prime (pre-spray) the device.
- Your neffy comes in a carton with 2 devices. You may need to use a second neffy if symptoms continue or get worse.
- You should always carry 2 neffy devices with you.
- Neffy is given as a single dose in either nostril. If a second dose of neffy is needed, it should be given in the same nostril, starting 5 minutes after the first dose.
- Do notsniff during or after receiving a dose of neffy.
- If any liquid drips out of the nose, you may not receive the full dose of medicine. If your symptoms continue or get worse, give a second dose of neffy in the same nostril, starting 5 minutes after the first dose.
- Important: If symptoms continue or get worse after the first dose of neffy, a second dose is needed, even if you did not see liquid drip out of the nose. Give the second dose in the same nostril, starting 5 minutes after the first dose.
- Get emergency help for further treatment of the anaphylactic episode, if needed, after using neffy. Before you receive neffy, your healthcare provider should talk to you about when to get emergency help.
- If you use too much neffy, call your healthcare provider or Poison Help line at 1-800-222-1222 or go to the nearest hospital emergency room right away.
- For more information and video instructions on the use of neffy, go to www.neffy.com or call 1-877-MY-NEFFY (1-877-696-3339).

What are the possible side effects of neffy?
Neffy may cause serious side effects.
If you have certain medical conditions, or take certain medicines, your condition may get worse or you may have more or longer lasting side effects when you use neffy.Talk to your healthcare provider about all your medical conditions.
Common side effects of neffy include:

- nasal discomfort
- throat irritation
- headache
- chest and nasal congestion
- feeling overly excited, nervous, or anxious
- nose bleed
- nose pain
- sneezing

- runny nose
- dry nose or throat
- tingling sensation, including in the nose
- feeling tired
- dizziness
- nausea
- vomiting

Tell your healthcare provider if you have any side effect that bothers you or that does not go away.
These are not all the possible side effects of neffy .For more information, ask your healthcare provider or pharmacist.
Call your doctor for medical advice about side effects. You may report side effects to FDA at 1-800-FDA-1088.

How should I store neffy?

- Store neffy nasal spray in the blister pack until ready to use.
- Store neffy at room temperature between 68°F to 77°F (20°C to 25°C).
- Do not freeze. If neffy freezes, the device will not spray.
- Storage of neffy at high temperatures up to 122°F (50°C) is allowed for a few days.
- Your neffy has an expiration date. Replace neffy before the expiration date.

Keep neffy and all medicines out of the reach of children.

General information about the safe and effective use of neffy.
Medicines are sometimes prescribed for purposes other than those listed in a Patient Information leaflet. Do not use neffy for a condition for which it was not prescribed. Do not give neffy to other people, even if they have the same symptoms that you have. It may harm them. You can ask your pharmacist or healthcare provider for information about neffy that is written for health professionals.

What are the ingredients in neffy?
Active Ingredient: epinephrine
Inactive Ingredients: benzalkonium chloride, disodium edetate, n-dodecyl beta-D-maltoside, sodium chloride, sodium metabisulfite, and hydrochloric acid or sodium hydroxide to adjust pH, in water for injection.

This Patient Information has been approved by the U.S. Food and Drug Administration

Revised: October 2025